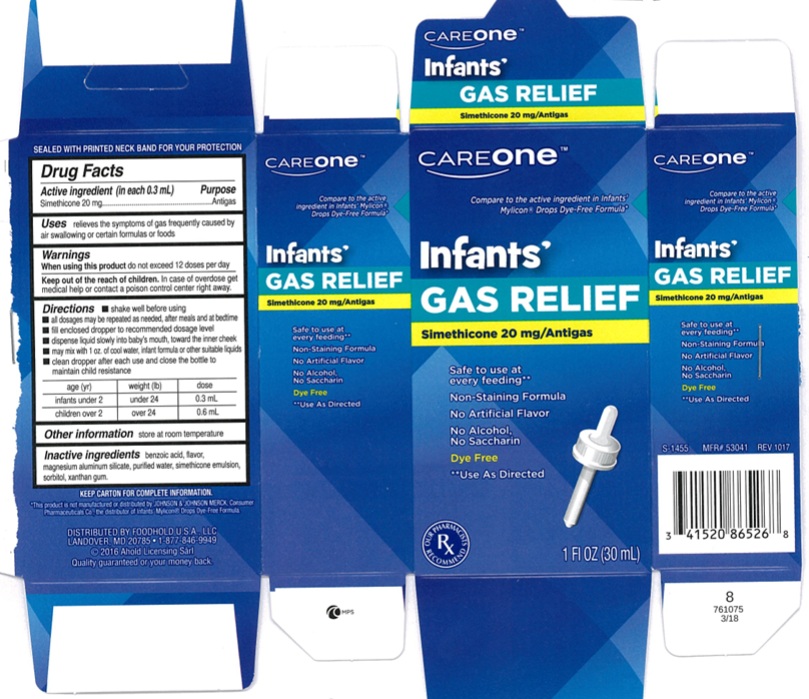 DRUG LABEL: Infants Non staining Gas relief
NDC: 72476-520 | Form: SOLUTION/ DROPS
Manufacturer: Retail Business Services, LLC.
Category: otc | Type: Human OTC Drug Label
Date: 20250227

ACTIVE INGREDIENTS: DIMETHICONE 20 mg/0.3 mL
INACTIVE INGREDIENTS: BENZOIC ACID; MAGNESIUM ALUMINUM SILICATE; WATER; SORBITOL; XANTHAN GUM

Infant's Non-Staining Gas Relief

ACTIVE INGREDIENT (in each 0.3 mL)

Simethicone 20 mg

PURPOSE

Antigas

USE(S)

relieves the symptoms of gas frequently caused by air swallowing or certain formulas or foods

WARNINGS

When using this product do not exceed 12 doses per day

KEEP OUT OF REACH OF CHILDREN

In case of overdose, get medical help or contact a Poison Control Center right away.

DIRECTIONS

- shake well before using
- all dosages may be repeated as needed, after meals and at bedtime
- fill enclosed dropper to recommended dosage level
- dispense liquid slowly into baby's mouth, toward the inner cheek
- may mix with 1 oz. of cool water, infant formula or other suitable liquids
- clean dropper after each use and close the bottle to maintain child resistance

age (yr) | weight (lb) | dose
infants under 2 | under 24 | 0.3 mL
children over 2 | over 24 | 0.6 mL

OTHER INFORMATION

store at room temperature

INACTIVE INGREDIENTS

benzoic acid, flavor, magnesium aluminum silicate, purified water, simethicone emulsion, sorbitol, xanthan gum

PRINCIPAL DISPLAY PANEL

CareOne™

Compare to the Active Ingredient in Mylicon® Drops Dye-Free Formula*

Infants'

GAS RELIEF

Simethicone 20 mg/Antigas

Safe to use at every feeding**

Non-staining Formula

No Artificial Flavor

No Alcohol

No Saccharine

Dye Free

**Use As Directed;

1 FL OZ (30mL)